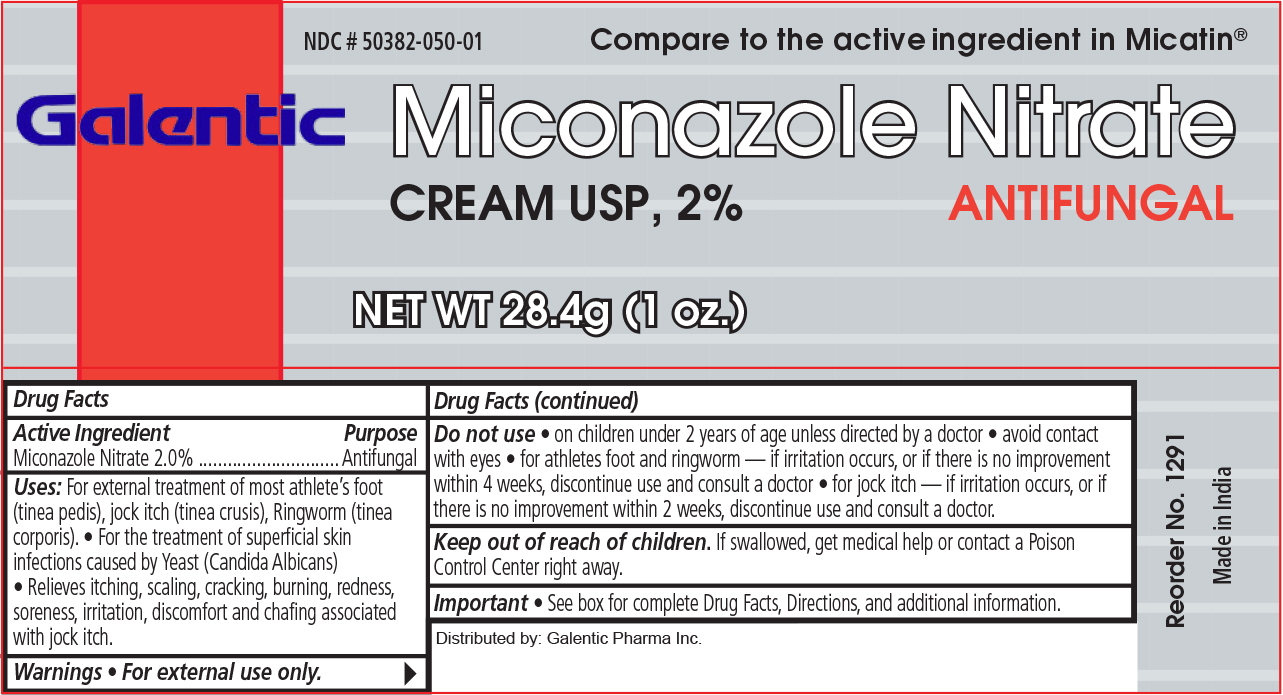 DRUG LABEL: MICONAZOLE
NDC: 50382-050 | Form: CREAM
Manufacturer: Galentic Pharma (India) Priva Te Limited
Category: otc | Type: HUMAN OTC DRUG LABEL
Date: 20130723

ACTIVE INGREDIENTS: MICONAZOLE NITRATE 20 mg/1 g
INACTIVE INGREDIENTS: CETETH-20; CETOSTEARYL ALCOHOL; CHLOROCRESOL; LIGHT MINERAL OIL; PROPYLENE GLYCOL; WATER; MINERAL OIL

Antifungal

Active Ingredient

Miconazole Nitrate 2%

Uses - Antifungal

- For treatment of most athlete's foot (tinea pedis), jock itch (tinea crusis), Ringworm (tinea corporis).
- For the treatment of superficial skin infections caused by Yeast (Candida Albicans).
- Relieves itching, scaling, cracking, burning, redness, soreness, irritation discomfort and chafing associated with jock itch.

Warnings

Do not use:

- Do not use on children under 2 years of age unless directed by a doctor.
- Avoid contact with eyes.
- For athletes foot and ringworm - if irritation occurs, or if there is no improvement within 4 weeks, discontinue use and consult a doctor.
- For jock itch - if irritation occurs, or if there is no improvement within two weeks, discontinue use and consult a doctor.
- Keep out of reach of children. If swallowed, get medical help or contact a Poison Control Center right away.

Directions

- Supervise children in the use of this product.
- If conditions persist longer, consult a doctor.
- This product is not effective on scalp or nails.

Other information.

Protect from freezing. Avoid excessive heat.

Directions

- Clean the affected area and dry thoroughly. Apply a layer of cream over affected area twice daily (morning and night) or as directed by a doctor.
- Foe athlete's foot and ringworm, use daily for 4 weeks.
- For jock itch, use daily for 2 weeks.
- For athlete's foot, pay special attention to spaces between toes: wear well fitting, ventilated shoes, and change shoes and socks at least once daily.

Inactive Ingredients

Inactive Ingredients: Cetomacrogol 1000, cetostearyl alcohol, chlorocresol, liquid paraffin, propylene glycol, purified water, white soft paraffin.

Keep Out of Reach of Children

- If swallowed get medical help or contact a Poison Control Center.

Principal Display Panel

Miconazole Nitrate Cream USP 2%

Gal Miconazole.jpg